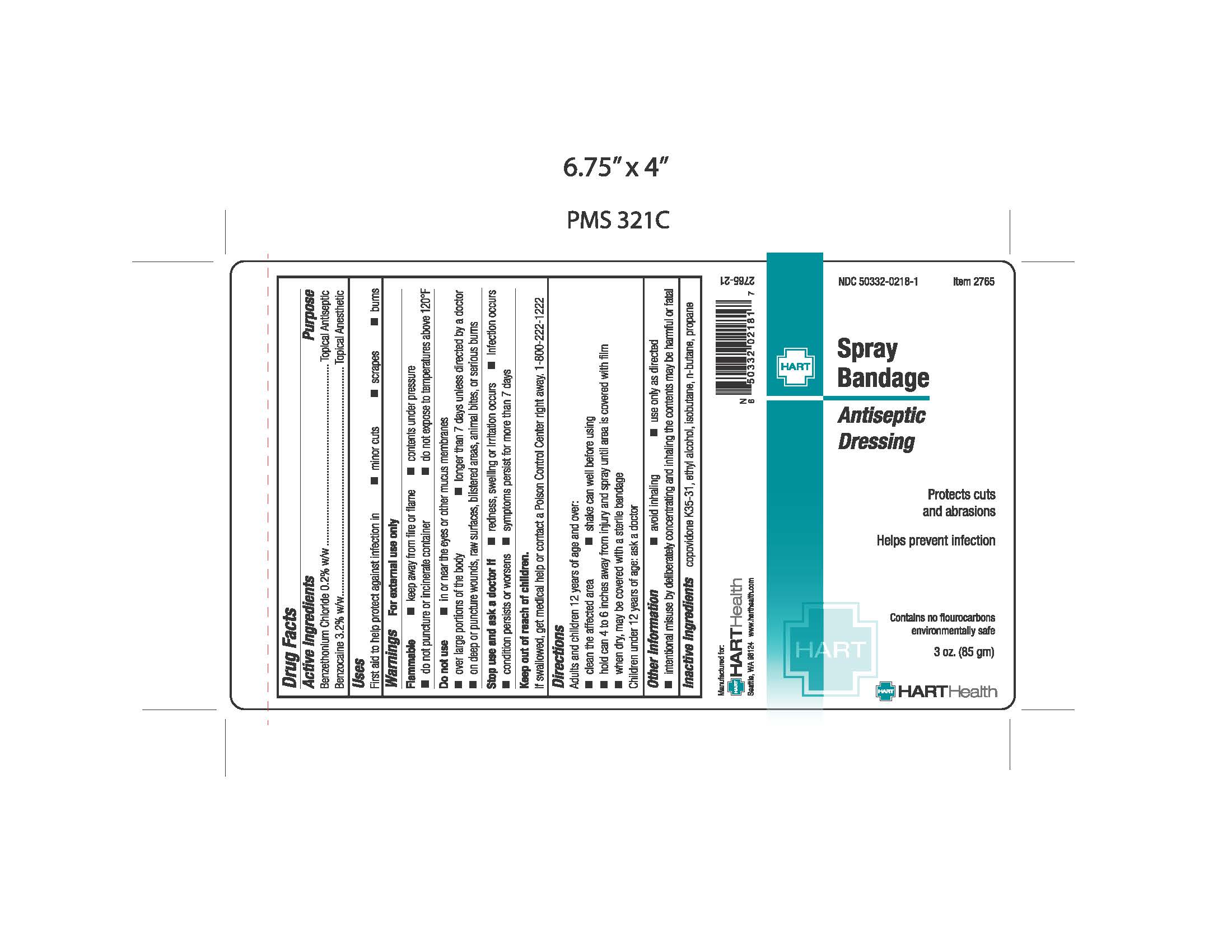 DRUG LABEL: Bandage
NDC: 50332-0218 | Form: AEROSOL, SPRAY
Manufacturer: HART Health
Category: otc | Type: HUMAN OTC DRUG LABEL
Date: 20260114

ACTIVE INGREDIENTS: BENZETHONIUM CHLORIDE 170 mg/85 g; BENZOCAINE 2720 mg/85 g
INACTIVE INGREDIENTS: ALCOHOL; COPOVIDONE K25-31; BUTANE; PROPANE; ISOBUTANE

Spray Bandage

Active Ingredients

Benzocaine 10% w/w
Benzethonium Chloride 0.2% w/w

Purpose

Topical Anesthetic
Topical Antiseptic

Uses

First aid to help protect against infection in

- minor cuts
- scrapes
- burns

Warnings

For External Use Only

Flammable

- keep away from fire or flame
- contents under pressure
- do not puncture or incinerate container
- do not expose to temperatures agove 120°F

Do not use

- in or near the eyes or other mucous membranes
- over large portions of the body
- longer than 7 days unless directed by a doctor
- on deep or puncture wounds, raw surfaces, blistered areas, animal bites, or serious burns

Stop use and ask doctor if

- redness, swelling, or irritation occurs
- infection occurs
- condition persists or worsens
- symptoms persist for more than 7 days

Keep out of reach of children

If swallowed, get medical help or contact a Poison Control Center right away. 1-800-222-1222

Directions

Adults and children 12 years of age and over:

- clean the affected area
- shake can well before using
- hold 4 to 6 inches from surface and spray until area is covered with film
- when dry, may be covered with a sterile bandage

Children under 12 years of age: ask a doctor

Other information

- avoid inhaling
- use only as directed
- intentional misuse by deliberately concentrating and inhaling the contents may be harmful or fatal

Inactive Ingredients

copovidone K35-31, ethyl alcohol, isobutane, n-butane, propane